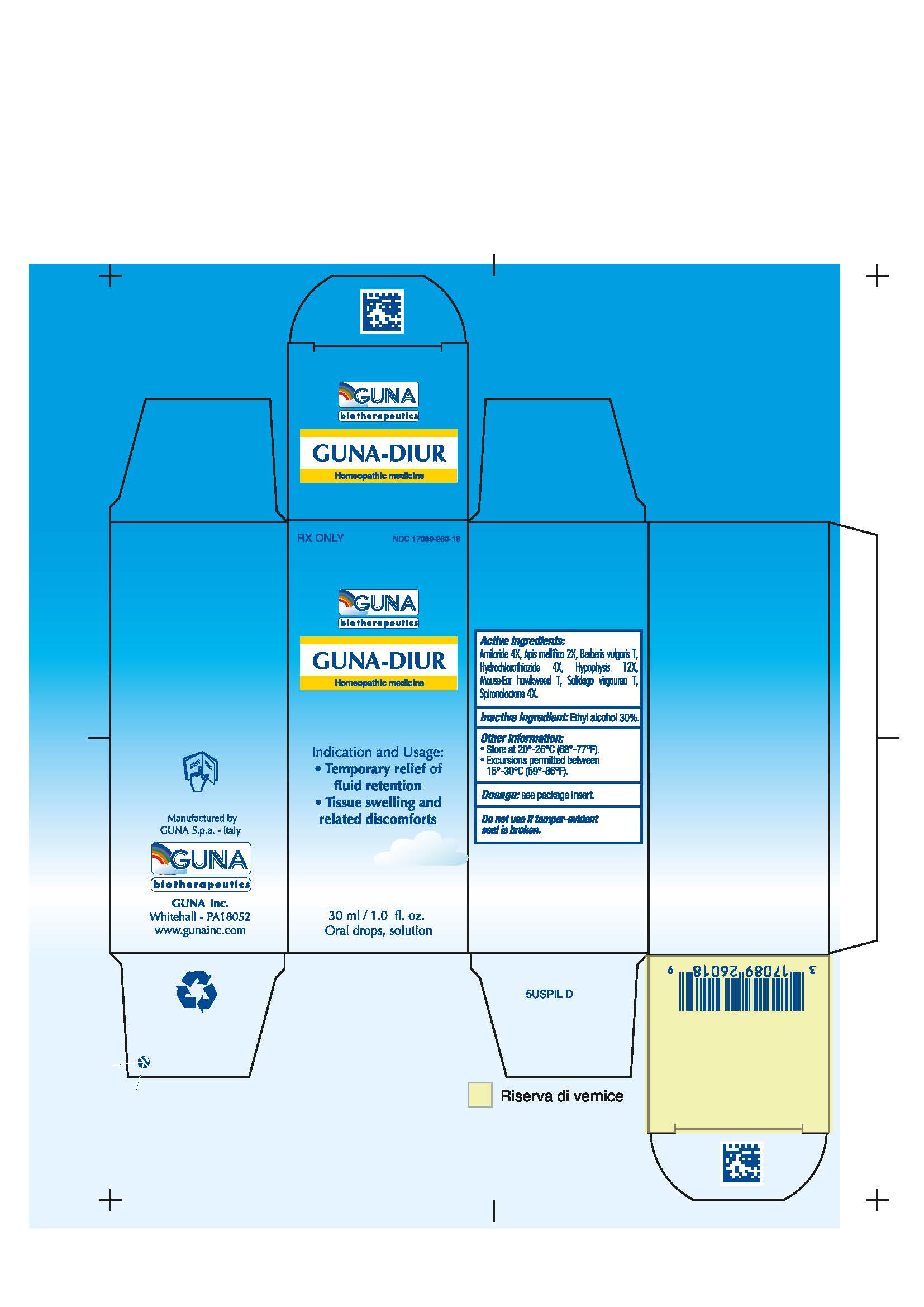 DRUG LABEL: GUNA-DIUR
NDC: 17089-260 | Form: SOLUTION/ DROPS
Manufacturer: Guna spa
Category: homeopathic | Type: HUMAN PRESCRIPTION DRUG LABEL
Date: 20181221

ACTIVE INGREDIENTS: AMILORIDE 4 [hp_X]/30 mL; APIS MELLIFERA 2 [hp_X]/30 mL; BERBERIS VULGARIS FRUIT 0.3 g/30 mL; HYDROCHLOROTHIAZIDE 4 [hp_X]/30 mL; SUS SCROFA PITUITARY GLAND 12 [hp_X]/30 mL; HIERACIUM PILOSELLA FLOWERING TOP 0.3 g/30 mL; SOLIDAGO VIRGAUREA FLOWERING TOP 0.3 g/30 mL; SPIRONOLACTONE 4 [hp_X]/30 mL
INACTIVE INGREDIENTS: ALCOHOL

GUNA®-DIUR

1. INDICATIONS AND USAGE

1.1 Temporary relief of fluid retention
1.2 Tissue swelling and related disconforts

2. DOSAGE AND ADMINISTRATION

Adults: 20 drops in a little water, 2 times per day for an avarage of two months.

Stop use and ask a doctor if symptoms persist more than 5 days.

Administration may very according to individual needs.

GUNA-DIUR may be used together with other homeopthic medicines.

3. DOSAGE FORMS AND STRENGTHS

3.1. 30 ml Bottle dropper container contains:
Active ingredients: Amiloride 4X 0.006 ml, Apis Mellifica 2X 0.626 ml, Berberis Vulgaris T 0.314 ml, Hydrochlorothiazide 4X 0.006 ml, Hypophysis 12X 6.314 ml, Mouse-Ear Hawkweed T 6.314 ml, Solidago Virgaurea T 0.314 ml, Spironolactone 4X 0.006 ml.
Inactive Ingredient: Ethylic Alcohol 30%

4. CONTRAINDICATIONS

4.1. There is no history of hypersensitivity to GUNA-DIUR. However, do not use if you are hypersensitive to any of the active ingredients of Guna-Diur.

5. WARNINGS AND PRECAUTIONS

5.1. GUNA-DIUR is contraindicated in patients with anuria and in patients with a history of hypersensitivity to Spironolactone, Amiloride, or Hydrocholorthiazide.
5.2. Use with caution in patients taking diuretic medications.

5.3 Keep out of reach of children.

6. ADVERSE REACTIONS

6.1. None known (see CONTRAINDICATIONS for hypersensitivity information).

7. DRUG INTERACTIONS

7.1. None Known

8. USE IN SPECIFIC POPULATIONS

8.1. Pregnancy: Pregnancy category C. Animal reproduction studies have not been conducted with GUNA-DIUR. GUNA®- DIUR should not be given to a pregnant woman.
8.2. Lactation: It is not known whether any of the ingredients in GUNA- DIUR are secreted in human milk. However, since many drugs are secreted in human milk, caution should be exercised when GUNA- DIUR is administered to a nursing woman.
8.3. Pediatric use: Safety and effectiveness in pediatric patients have not been established.

8.4. Geriatric use: No restrictions.

9. DRUG ABUSE AND DEPENDENCE

9.1. No Known.

10. OVERDOSAGE

10.1. No Known.

11. DESCRIPTION

11. 1 GUNA-DIUR is a homeopathic medicine indicated for the temporary relief of fluid retention, tissue swelling and related disconforts.

12. CLINICAL PHARMACOLOGY

12.1. GUNA-DIUR exerts a diuretic effect. This is based on homeopthica Materia Medica and homeopathic principles.
12.2. Pharmacodynamics
Not applicable to homeopthic medicinal products.

12.3. Pharmacokinetics

Not applicable to homeopthic medicinal products.

13. NONCLINICAL TOXICOLOGY

13.1. Not available.

14. CLINICAL STUDIES

14.1. GUNA-DIUR efficacy is not supported by clinical studies. It is based on homeopathic Materia Medica and scientific literature.

15. REFERENCES

15.1. H.H. Reckeweg. Homeopathic Materia Medica. Aurelia Verlag.
15.2. Boericke, William, Materia Medica with Reperatory, 1927, ninth edition

16. HOW SUPPLIED/STORAGE AND HANDLING

16.1. NDC 17089-260-18 Oral Solution/Drops 30 mL
16.2. Store at 20-25°C (68-77° F). Excursions permitted between 15°-30°C (59°-86°F).

17. PATIENT COUNSELING INFORMATION

17.1. Patients should be informed about Homeopathy and the main differences with conventional clinical approaches.